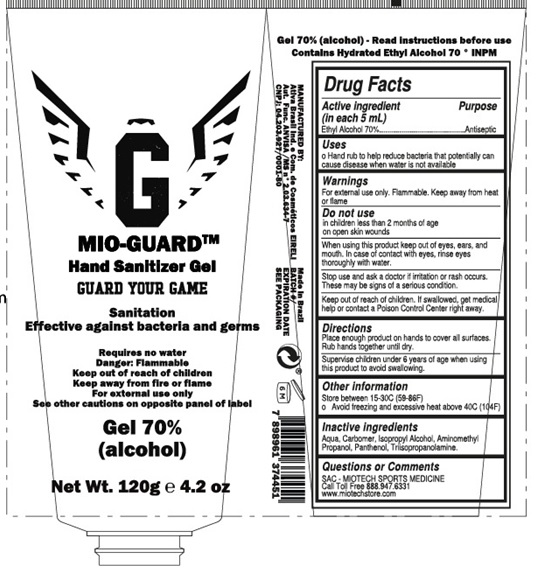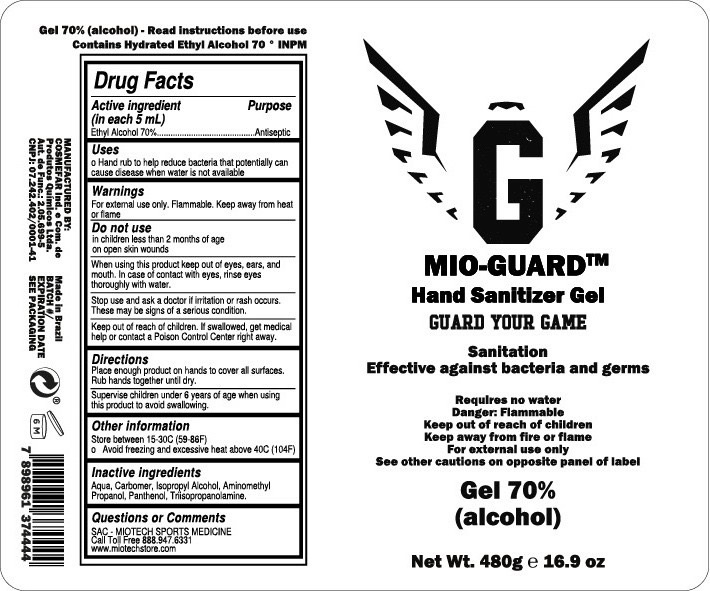 DRUG LABEL: Mio Guard Hand Sanitizer
NDC: 75533-070 | Form: GEL
Manufacturer: MIO-GUARD LLC
Category: otc | Type: HUMAN OTC DRUG LABEL
Date: 20200422

ACTIVE INGREDIENTS: ALCOHOL 70 mL/100 mL
INACTIVE INGREDIENTS: WATER; CARBOMER HOMOPOLYMER, UNSPECIFIED TYPE; ISOPROPYL ALCOHOL; AMINOMETHYLPROPANOL; PANTHENOL; TRIISOPROPANOLAMINE

Active Ingredient

Ethyl Alcohol 70%

Purpose

Antiseptic

Use

Hand rub to help reduce bacteria that potentially can cause disease when water is not available.

Warnings

For external use only. Flammable. Keep away from heat or flame

Do not use

- in children less than 2 months of age
- on open skin wounds

When using this product

Keep out of eyes, ears, and mouth. In case of contact with eyes, rinse eyes thoroughly with water.

Stop use and ask a doctor if

Irritation or rash occurs. These may be signs of a serious condition.

Keep out of reach of children.

If swallowed, get medical help or contact a Poison Control Center right away.

Directions

- Place enough product on hands to cover all surfaces. Rub hands together until dry.
- Supervise children under 6 years of age when using this product to avoid swallowing.

Other information

- Store between 15-30C (59-86F)
- Avoid freezing and excessive heat above 40C (104F)

Inactive ingredients

Aqua, Carbomer, Isopropyl Alcohol, Aminomethyl Propanol, Panthenol, Triisopropanolamine

Questions or Comments

SAC - MIOTECH SPORTS MEDICINE

Call Toll Free: 888-947-6331

www.miotechstore.com

Principal Display Panel

NDC: 75533-070-04

MIO-GUARDTM

Hand Sanitizer Gel

GUARD YOUR GAME

Sanitation Effective against bacteria and germs

Requires no water

Danger: Flammable

Keep out of reach of children

Keep away from fire or flame

For external use only

See other cautions on opposite panel of label

Gel 70% (alcohol)

Net Wt. 120g e 4.2 oz

NDC: 75533-070-16

MIO-GUARDTM

Hand Sanitizer Gel

GUARD YOUR GAME

Sanitation Effective against bacteria and germs

Requires no water

Danger: Flammable

Keep out of reach of children

Keep away from fire or flame

For external use only

See other cautions on opposite panel of label

Gel 70% (alcohol)

Net Wt. 480g e 16.9 oz